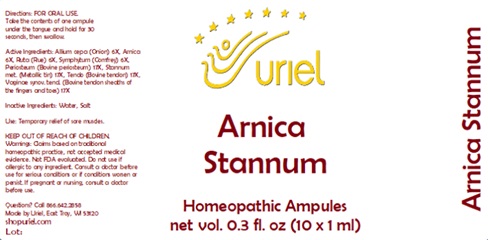 DRUG LABEL: Arnica Stannum
NDC: 48951-1157 | Form: LIQUID
Manufacturer: Uriel Pharmacy Inc.
Category: homeopathic | Type: HUMAN OTC DRUG LABEL
Date: 20231122

ACTIVE INGREDIENTS: ONION 6 [hp_X]/1 mL; ARNICA MONTANA 6 [hp_X]/1 mL; RUTA GRAVEOLENS FLOWERING TOP 6 [hp_X]/1 mL; COMFREY ROOT 6 [hp_X]/1 mL; BOS TAURUS BONE 17 [hp_X]/1 mL; TIN 17 [hp_X]/1 mL; BOS TAURUS TENDON 17 [hp_X]/1 mL
INACTIVE INGREDIENTS: WATER; SODIUM CHLORIDE

Arnica Stannum

INDICATIONS AND USAGE

Directions: FOR ORAL USE.

DOSAGE AND ADMINISTRATION

Take the contents of one ampule under the tongue and hold for 30 seconds, then swallow.

ACTIVE INGREDIENT

Active Ingredients: Allium cepa (Onion) 6X, Arnica 6X, Ruta (Rue) 6X, Symphytum (Comfrey) 6X, Periosteum (Bovine periosteum) 17X, Stannum met. (Metallic tin) 17X, Tendo (Bovine tendon) 17X,
Vaginae synov. tend. (Bovine tendon sheaths of the fingers and toes) 17

Inactive Ingredients: Water, Salt

PURPOSE

Use: Temporary relief of sore muscles.

KEEP OUT OF REACH OF CHILDREN.

WARNINGS

Warnings: Claims based on traditional homeopathic practice, not accepted medical evidence. Not FDA evaluated. Do not use if allergic to any ingredient. Consult a doctor before use for serious conditions or if conditions worsen or persist. If pregnant or nursing, consult a doctor before use.

Questions? Call 866.642.2858
Made by Uriel, East Troy, WI 53120
shopuriel.com